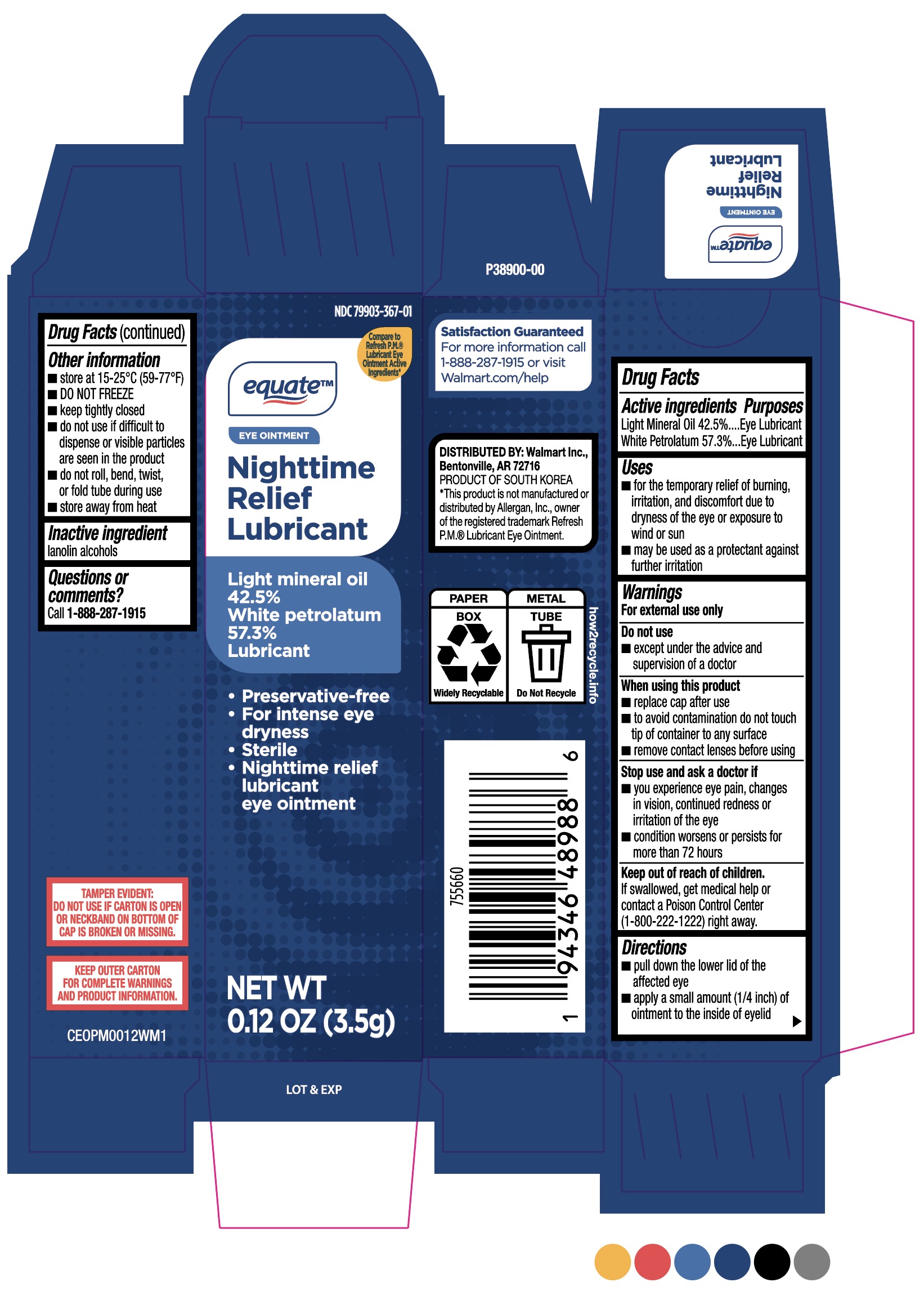 DRUG LABEL: Equate Nighttime Relief Lubricant
NDC: 11716-0367 | Form: OINTMENT
Manufacturer: Hanlim Pharm Co. LTD
Category: otc | Type: HUMAN OTC DRUG LABEL
Date: 20251222

ACTIVE INGREDIENTS: LIGHT MINERAL OIL 425 mg/1 g; WHITE PETROLATUM 573 mg/1 g
INACTIVE INGREDIENTS: LANOLIN ALCOHOLS

Hanlim (MFR) for Walmart (PLD) NDC: 79903-367-01
Equate Nighttime Relief Lubricant

PURPOSE

Eye Lubricant

Keep out of reach of children. If swallowed, get medical help or contact a Poison Control Center
(1-800-222-1222) right away.

WARNING

For External Use Only

Do not use

■ except under the advice and supervision of a doctor

When using this product

■replace cap after use to avoid contamination
■do not touch tip of container to any surface remove contact lenses before using
Stop use and ask a doctor if
■ you experience eye pain, changes in vision, continued redness or irritation of the eye
condition worsens or persists for more than 72 hours

Active ingredients

Light Mineral Oil 42.5%

White Petrolatum 57.3%

Inactive Ingredients

Lanolin alcohols

Directions:
pull down the lower lid of the affected eye
apply a small amount (1/4 inch) of ointment to the inside of eyelid

Other information

■ Store at 15-25°C (59-77 °F)
■ DO NOT FREEZE
■ keep tightly closed
■ do not use if difficult to dispense or visible particles are seen in the product

■ do not roll, bend, twist, or fold tube during use

■ store away from heat

Uses
■ for the temporary relief of burning, irritation, and discomfort due to dryness of the eye or exposure to
wind or sun
■ may be used as a protectant against further irritation